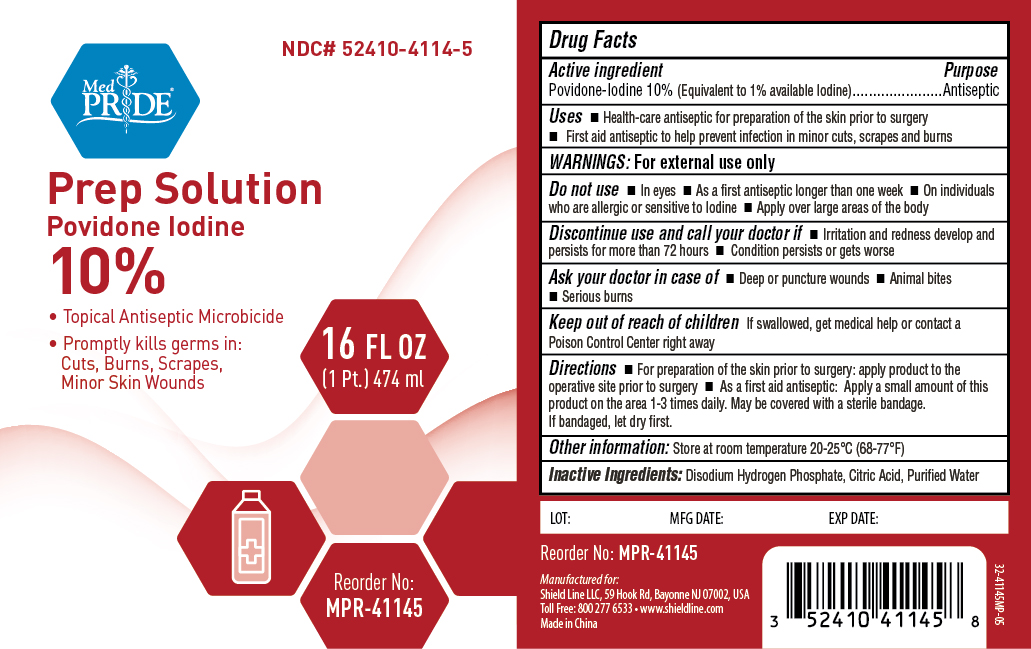 DRUG LABEL: MedPride Prep Solution
NDC: 52410-4114 | Form: SOLUTION
Manufacturer: Shield Line LLC
Category: otc | Type: HUMAN OTC DRUG LABEL
Date: 20250818

ACTIVE INGREDIENTS: POVIDONE-IODINE 100 mg/1 mL
INACTIVE INGREDIENTS: GLYCERIN; POLYSORBATE 80; CITRIC ACID MONOHYDRATE; SODIUM CITRATE, UNSPECIFIED FORM; SODIUM PHOSPHATE, DIBASIC, ANHYDROUS; WATER

Medpride Prep Solution Topical Antiseptic Microbicide

Active Ingredient

Povidone Iodine, 10% (equivalent to 1% available Iodine)

Purpose

Antiseptic

Uses

- Health-care antiseptic for preparation of the skin prior to surgery
- First aid antiseptic to help prevent infection in minor cuts, scrapes and burns

Warnings

For External Use Only

Do not use

- In eyes
- As a first antiseptic longer than one week
- On individuals who are allergic or sensitive to iodine
- Apply over large areas of body

Discontinue use and call your doctor if

- Irritation and redness develop and persists for more than 72 hours
- Condition persists or get worse

Ask your doctor in case of

- Deep or puncture wounds
- Animal bites
- Serious burns

Keep out of reach of children

If swallowed, get medical help or contact a Poison Control Center right away.

Directions

For preparation of the skin prior to surgery:

- Apply product to the operative site prior to surgery

As a first aid antiseptic:

- Clean the affected area
- Apply a small amount of this product on the area 1-3 times daily
- May be covered with a sterile bandage
- If bandaged, let dry first

Inactive ingredients

Citric Acid, Sodium Citrate, Glycerin, Tween 80, Disodium Phosphate, Purified Water